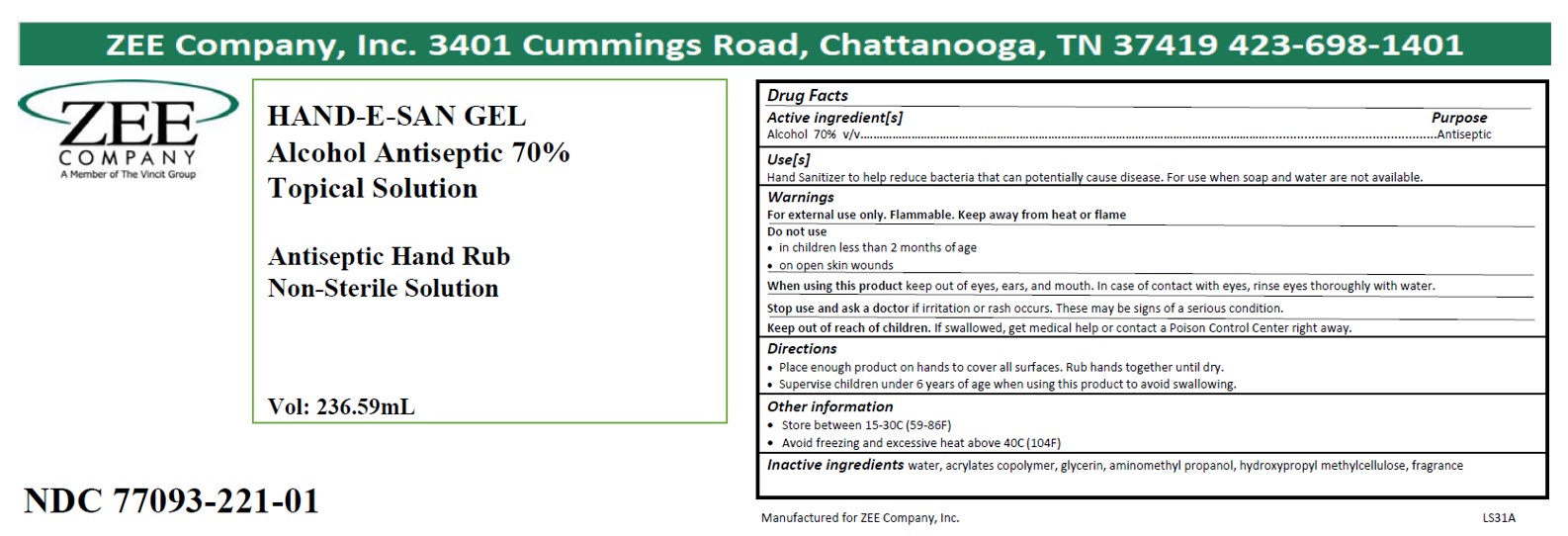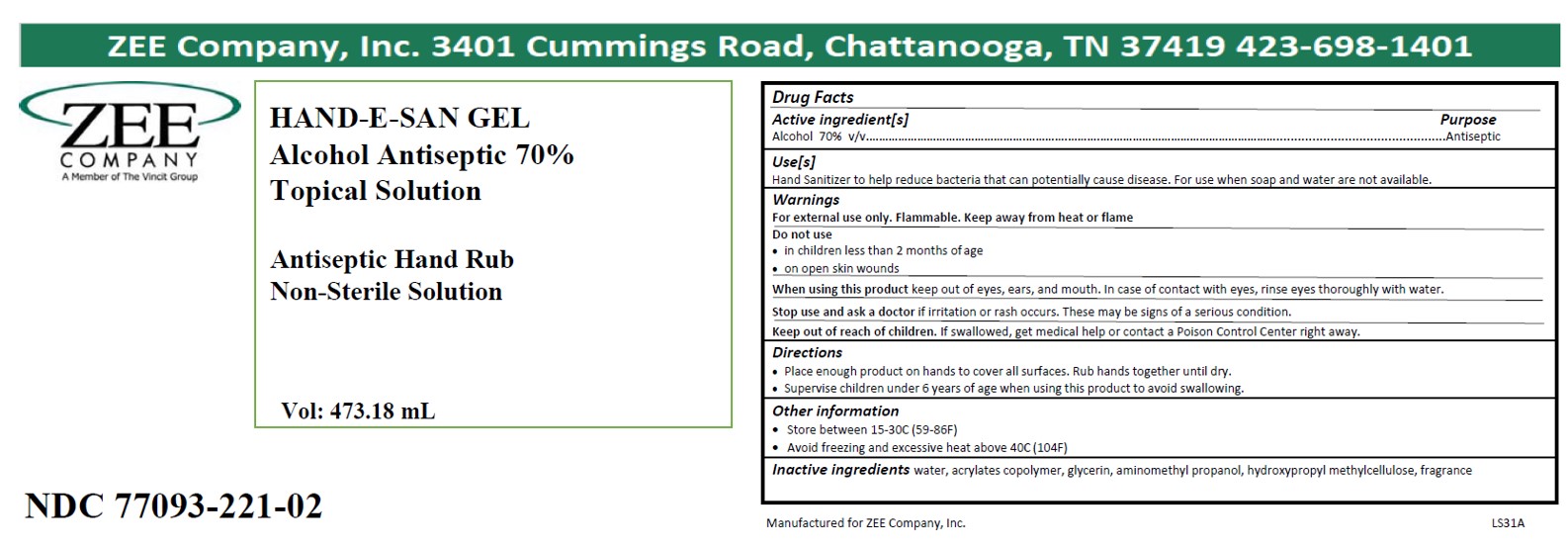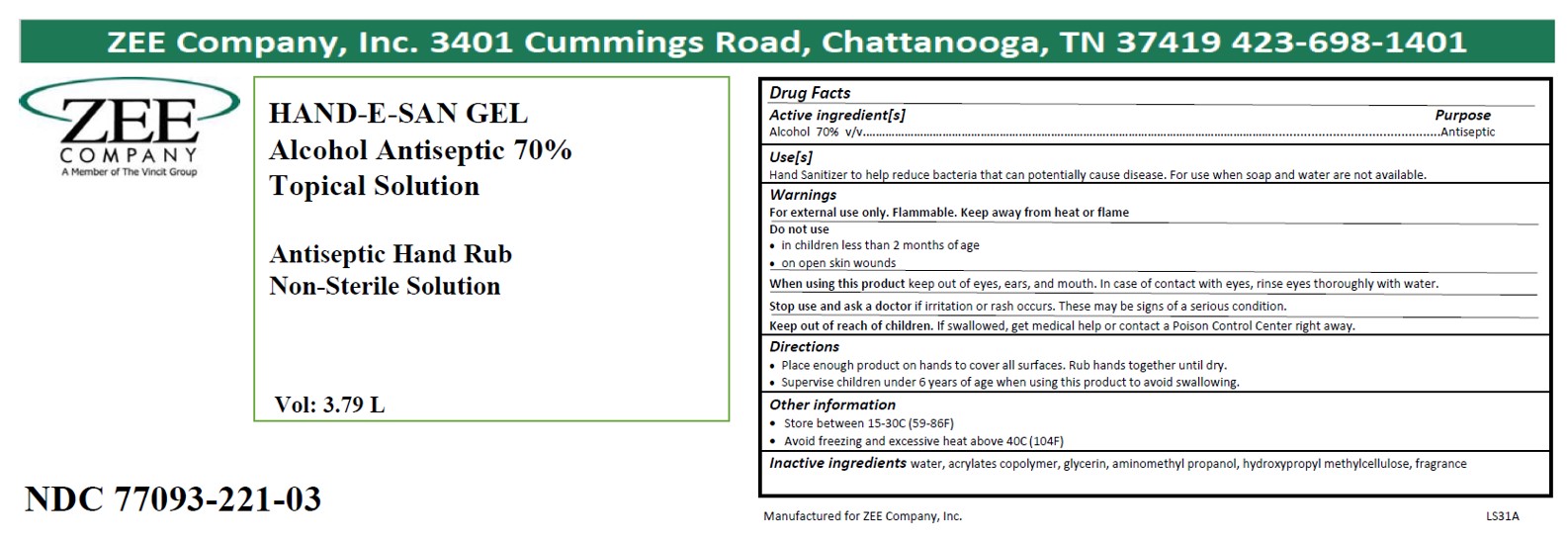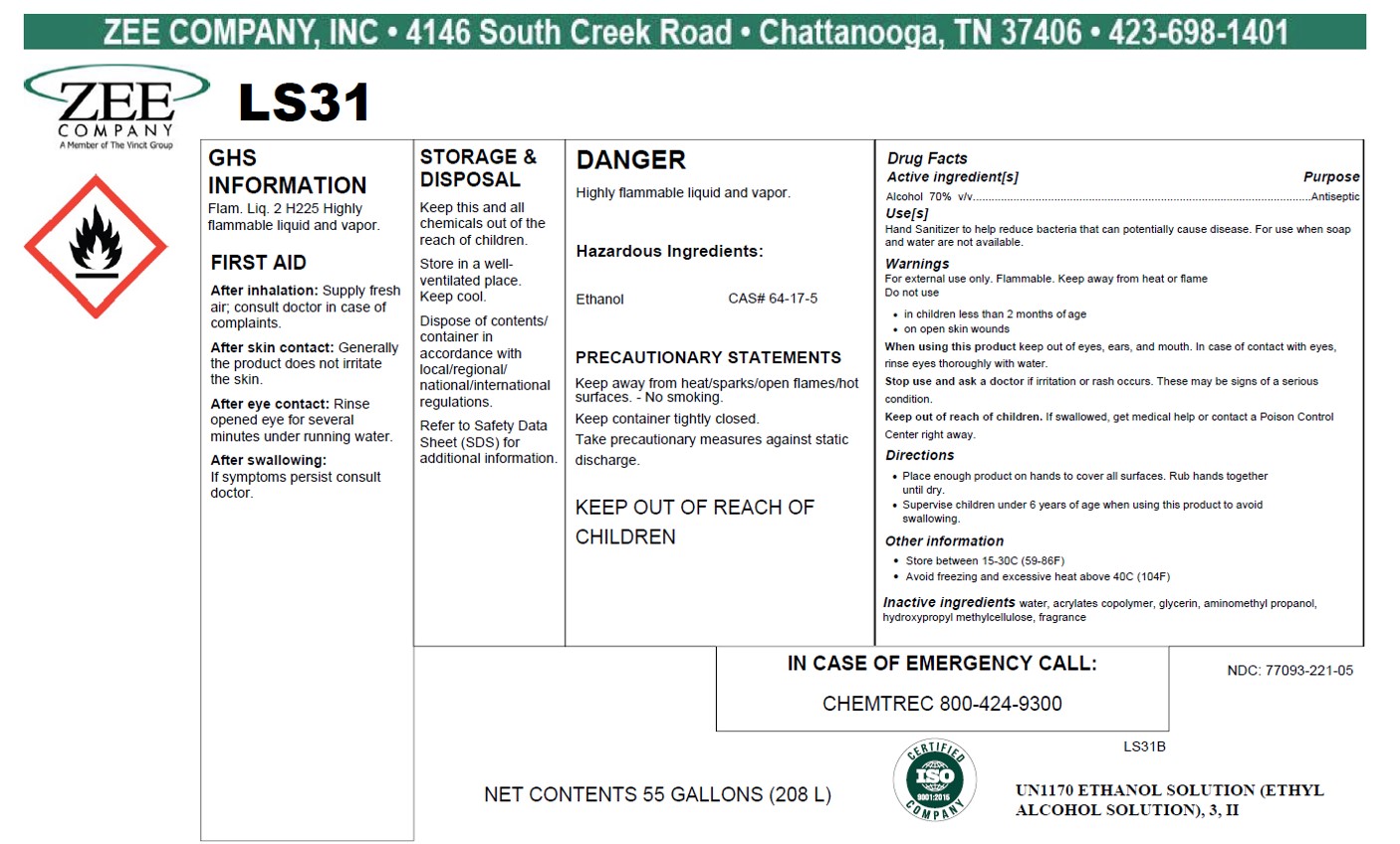 DRUG LABEL: LS31
NDC: 77093-221 | Form: LIQUID
Manufacturer: Vincit Zee Company
Category: otc | Type: HUMAN OTC DRUG LABEL
Date: 20200730

ACTIVE INGREDIENTS: ALCOHOL 70 mL/100 mL
INACTIVE INGREDIENTS: HYPROMELLOSES; GLYCERIN; WATER; AMINOMETHYLPROPANOL; METHACRYLIC ACID - ETHYL ACRYLATE COPOLYMER (4500 MPA.S)

LS31 Cummings Rd.

active ingredient

Alcohol

purpose

Antiseptic

INDICATIONS AND USAGE

Keep out of eyes, ears, and mouth. In case of contact with eyes, rinse eyes thoroughly with water.

WARNINGS

For external use only. Flammable. Keep away from heat and open flame.

Do not use on children less than 2 months of age or on open skin wounds.

WHEN USING

Keep out of eyes, ears, and mouth. In case of contact with eyes, rinse eyes thoroughly with water.

Stop use and ask a doctor if irritation or rash occurs. These may be signs of a serious condition.

Keep out of reach of children. If swallowed get medical help or contact a Poison Control Center right away.

DOSAGE AND ADMINISTRATION

Place enough product on hands to cover all surfaces. Rub hands together until dry.

Supervise children under 6 years of age when using this product to avoid swallowing.

other safety information

Store between 15-30C (59-86F). Avoid freezing and excessive heat above 40C (104F)

INACTIVE INGREDIENT

water, acrylates copolymer, glycerin, aminomethyl propanol, hydroxypropyl methylcellulose, fragrance

LS31 Product Labels

263.59 ml: NDC Code 77093-221-01

473.18 ml: NDC Code 77093-221-02

3785ml : NDC Code 77093-221-03

208000ml: NDC Code 77093-221-05